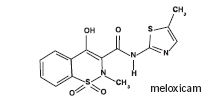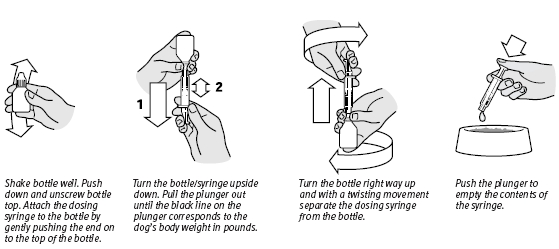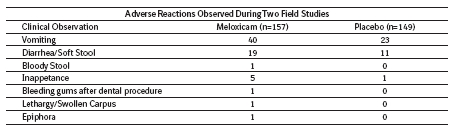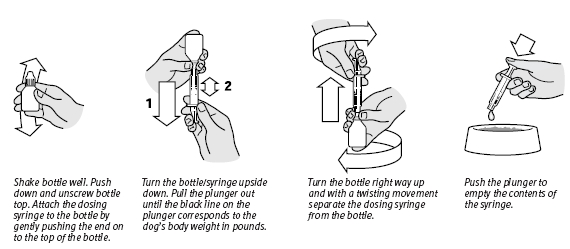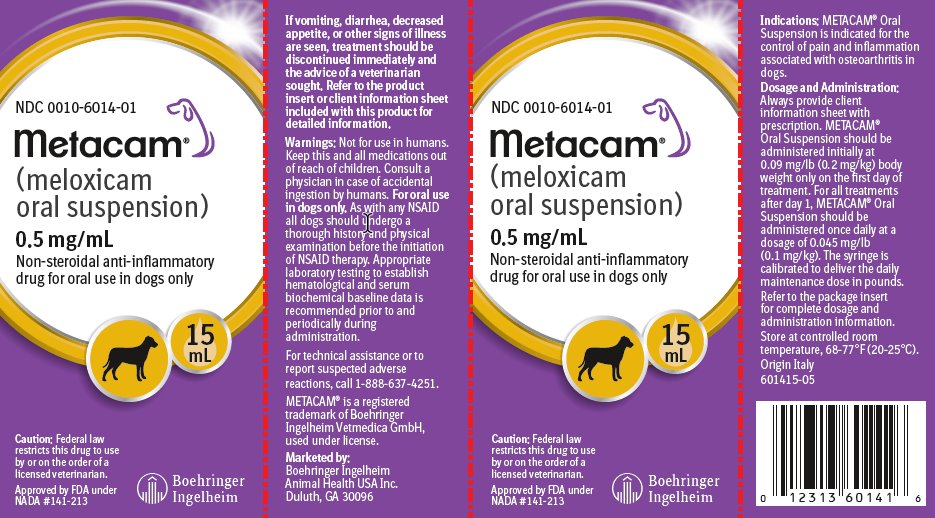 DRUG LABEL: Metacam
NDC: 0010-6014 | Form: SUSPENSION
Manufacturer: Boehringer Ingelheim Animal Health USA Inc.
Category: animal | Type: PRESCRIPTION ANIMAL DRUG LABEL
Date: 20250502

ACTIVE INGREDIENTS: MELOXICAM 0.05 g/100 mL
INACTIVE INGREDIENTS: SILICON DIOXIDE; SODIUM BENZOATE; SORBITOL; GLYCERIN; SACCHARIN SODIUM; XYLITOL; SODIUM PHOSPHATE, MONOBASIC, DIHYDRATE; CITRIC ACID MONOHYDRATE; HYDROXYETHYL CELLULOSE (2000 MPA.S AT 1%)

Metacam®
(meloxicam oral suspension)
0.5 mg/mL

(equivalent to 0.02 mg per drop)

Non-steroidal anti-inflammatory drug for oral use in dogs only

Caution:

Federal law restricts this drug to use by or on the order of a licensed veterinarian.

Warning:

Repeated use of meloxicam in cats has been associated with acute renal failure and death. Do not administer additional injectable or oral meloxicam to cats. See Contraindications, Warnings, and Precautions for detailed information.

Description:

Meloxicam is a non-steroidal anti-inflammatory drug (NSAID) of the oxicam class. Each milliliter of METACAM Oral Suspension contains meloxicam equivalent to 0.5 milligrams and sodium benzoate (1.5 milligrams) as a preservative. The chemical name for Meloxicam is 4-Hydroxy-2-methyl-N-(5-methyl-2-thiazolyl)-2H-1,2-benzothiazine-3-carboxamide-1, 1-dioxide. The formulation is a yellowish viscous suspension with the odor of honey.

Indications:

METACAM Oral Suspension is indicated for the control of pain and inflammation associated with osteoarthritis in dogs.

Dosage and Administration:

Always provide client information sheet with prescription. Carefully consider the potential benefits and risk of METACAM and other treatment options before deciding to use METACAM. Use the lowest effective dose for the shortest duration consistent with individual response. METACAM Oral Suspension should be administered initially at 0.09 mg/lb (0.2 mg/kg) body weight only on the first day of treatment. For all treatments after day 1, METACAM Oral Suspension should be administered once daily at a dose of 0.045 mg/lb (0.1 mg/kg). The syringe is calibrated to deliver the daily maintenance dose in pounds.

Directions for Administration:

Dogs under 10 pounds (4.5 kg)

Shake well before use, then remove cap. Particular care should be given with regard to the accuracy of dosing. To prevent accidental overdosing of small dogs, administer drops on food only, never directly into the mouth. Carefully measure suspension onto food to assure that the correct dose is given before presentation of the food to the dog. The syringe provided with the meloxicam concentration of 0.5 mg/mL cannot be used to measure doses for dogs weighing less than 2 lbs (0.90 kg).

For dogs less than 2 lbs (0.90 kg), METACAM Oral Suspension can be given using the dropper bottle: two drops for each pound of body weight for the 0.5 mg/mL concentration (five drops for each kilogram of body weight), dropped directly onto the food.

For dogs between 2 - 10 pounds, METACAM Oral Suspension can be given by drops or by using the measuring syringe provided in the package (see dosing procedure in the next column). The syringe fits on to the bottle and has a scale beginning at 2 lbs, designed to deliver the daily maintenance dose (0.05 mg/lb or 0.1 mg/kg). When using the syringe, the dog’s weight should be rounded down to the nearest 1 pound increment. Replace and tighten cap after use.

Dogs over 10 pounds (4.5 kg)

Shake well before use then remove cap. METACAM Oral Suspension may be either mixed with food or placed directly into the mouth. Particular care should be given with regard to the accuracy of dosing. METACAM Oral Suspension can be given using the measuring syringe provided in the package (see dosing procedure in the next column). The syringe fits on to the bottle and has a scale in pounds designed to deliver the daily maintenance dose (0.05 mg/lb or 0.1 mg/kg). When using the syringe, the dog’s weight should be rounded down to the nearest 1 pound increment. Alternatively, METACAM Oral Suspension can be given using the dropper bottle: two drops for each pound of body weight for the 0.5 mg/mL concentration (five drops for each kilogram of body weight). Replace and tighten cap after use.

Contraindications:

Dogs with known hypersensitivity to meloxicam should not receive METACAM Oral Suspension. Do not use METACAM Oral Suspension in cats. Acute renal failure and death have been associated with the use of meloxicam in cats.

Warnings:

Not for use in humans. Keep this and all medications out of reach of children. Consult a physician in case of accidental ingestion by humans. For oral use in dogs only.

As with any NSAID all dogs should undergo a thorough history and physical examination before the initiation of NSAID therapy. Appropriate laboratory testing to establish hematological and serum biochemical baseline data is recommended prior to and periodically during administration. Owner should be advised to observe their dog for signs of potential drug toxicity and be given a client information sheet about METACAM.

Precautions:

The safe use of METACAM Oral Suspension in dogs younger than 6 months of age, dogs used for breeding, or in pregnant or lactating dogs has not been evaluated. Meloxicam is not recommended for use in dogs with bleeding disorders, as safety has not been established in dogs with these disorders.

As a class, cyclo-oxygenase inhibitory NSAIDs may be associated with gastrointestinal, renal and hepatic toxicity. Sensitivity to drug-associated adverse events varies with the individual patient. Dogs that have experienced adverse reactions from one NSAID may experience adverse reactions from another NSAID. Patients at greatest risk for renal toxicity are those that are dehydrated, on concomitant diuretic therapy, or those with existing renal, cardiovascular, and/or hepatic dysfunction. Concurrent administration of potentially nephrotoxic drugs should be carefully approached. NSAIDs may inhibit the prostaglandins that maintain normal homeostatic function. Such anti-prostaglandin effects may result in clinically significant disease in patients with underlying or pre-existing disease that has not been previously diagnosed. Since NSAIDs possess the potential to induce gastrointestinal ulcerations and/or perforations, concomitant use with other anti-inflammatory drugs, such as NSAIDs or corticosteroids, should be avoided. If additional pain medication is needed after administration of the total daily dose of METACAM Oral Suspension, a non-NSAID or non-corticosteroid class of analgesia should be considered. The use of another NSAID is not recommended. Consider appropriate washout times when switching from corticosteroid use or from one NSAID to another in dogs. The use of concomitantly protein-bound drugs with METACAM Oral Suspension has not been studied in dogs. Commonly used protein-bound drugs include cardiac, anticonvulsant and behavioral medications. The influence of concomitant drugs that may inhibit metabolism of METACAM Oral Suspension has not been evaluated. Drug compatibility should be monitored in patients requiring adjunctive therapy.

Adverse Reactions:

Field safety was evaluated in 306 dogs. Based on the results of two studies, GI abnormalities (vomiting, soft stools, diarrhea, and inappetence) were the most common adverse reactions associated with the administration of meloxicam. The following table lists adverse reactions and the numbers of dogs that experienced them during the studies. Dogs may have experienced more than one episode of the adverse reaction during the study.

In foreign suspected adverse drug reaction (SADR) reporting over a 9 year period, incidences of adverse reactions related to meloxicam administration included: auto-immune hemolytic anemia (1 dog), thrombocytopenia (1 dog), polyarthritis (1 dog), nursing puppy lethargy (1 dog), and pyoderma (1 dog).

Post-Approval Experience (Rev. 2010):

The following adverse events are based on post-approval adverse drug experience reporting. Not all adverse reactions are reported to FDA/CVM. It is not always possible to reliably estimate the adverse event frequency or establish a causal relationship to product exposure using these data. The following adverse events are listed in decreasing order of frequency by body system.

Gastrointestinal: vomiting, anorexia, diarrhea, melena, gastrointestinal ulceration

Urinary: azotemia, elevated creatinine, renal failure

Neurological/Behavioral: lethargy, depression

Hepatic: elevated liver enzymes

Dermatologic: pruritus

Death has been reported as an outcome of the adverse events listed above. Acute renal failure and death have been associated with use of meloxicam in cats.

To report suspected adverse drug events, for technical assistance or to obtain a copy of the SDS, contact Boehringer Ingelheim Animal Health USA Inc. at 1-888-637-4251. For additional information about adverse drug experience reporting for animal drugs, contact FDA at 1-888-FDA-VETS or online at www.fda.gov/reportanimalae.

Information for Dog Owners:

METACAM, like other drugs of its class, is not free from adverse reactions. Owners should be advised of the potential for adverse reactions and be informed of the clinical signs associated with drug intolerance. Adverse reactions may include vomiting, diarrhea, decreased appetite, dark or tarry stools, increased water consumption, increased urination, pale gums due to anemia, yellowing of gums, skin or white of the eye due to jaundice, lethargy, incoordination, seizure, or behavioral changes. Serious adverse reactions associated with this drug class can occur without warning and in rare situations result in death (see Adverse Reactions). Owners should be advised to discontinue METACAM and contact their veterinarian immediately if signs of intolerance are observed.

The vast majority of patients with drug related adverse reactions have recovered when the signs are recognized, the drug is withdrawn, and veterinary care, if appropriate, is initiated. Owners should be advised of the importance of periodic follow up for all dogs during administration of any NSAID.

Clinical Pharmacology:

Meloxicam has nearly 100% bioavailability when administered orally with food. The terminal elimination half life after a single dose is estimated to be approximately 24 hrs (+/-30%) regardless of route of administration. There is no evidence of statistically significant gender differences in drug pharmacokinetics. Drug bioavailability, volume of distribution, and total systemic clearance remain constant up to 5 times the recommended dose for use in dogs. However, there is some evidence of enhanced drug accumulation and terminal elimination half-life prolongation when dogs are dosed for 45 days or longer.

Peak drug concentrations can be expected to occur within about 7.5 hrs after oral administration. Corresponding peak concentration is approximately 0.464 mcg/mL following a 0.2 mg/kg oral dose. The drug is 97% bound to canine plasma proteins.

Effectiveness:

The effectiveness of meloxicam was demonstrated in two field studies involving a total of 277 dogs representing various breeds, between six months and sixteen years of age, all diagnosed with osteoarthritis. Both of the placebo-controlled, masked studies were conducted for 14 days. All dogs received 0.2 mg/kg meloxicam on day 1. All dogs were maintained on 0.1 mg/kg oral meloxicam from days 2 through 14 of both studies. Parameters evaluated by veterinarians included lameness, weight-bearing, pain on palpation, and overall improvement. Parameters assessed by owners included mobility, ability to rise, limping, and overall improvement.

In the first field study (n=109), dogs showed clinical improvement with statistical significance after 14 days of meloxicam treatment for all parameters. In the second field study (n=48), dogs receiving meloxicam showed a clinical improvement after 14 days of therapy for all parameters; however, statistical significance was demonstrated only for the overall investigator evaluation on day 7, and for the owner evaluation on day 14.

Palatability:

METACAM Oral Suspension was accepted by 100% of the dogs when veterinarians administered the initial dose into the mouth. METACAM Oral Suspension was accepted by 90% of the dogs (123/136) when administered by owners. Problems associated with administration included refusal of food, resistance to swallowing and salivation.

Safety:

Six Week Study

In a six week target animal safety study, meloxicam was administered orally at 1, 3, and 5X the recommended dose with no significant clinical adverse reactions. Animals in all dose groups (control, 1, 3 and 5X the recommended dose) exhibited some gastrointestinal distress (diarrhea and vomiting). No treatment-related changes were observed in hematological, blood chemistry, urinalysis, clotting time, or buccal mucosal bleeding times.

Necropsy results included stomach mucosal petechiae in one control dog, two dogs at the 3X and one dog at the 5X dose. Other macroscopic changes included areas of congestion or depression of the mucosa of the jejunum or ileum in three dogs at the 1X dose and in two dogs at the 5X dose. Similar changes were also seen in two dogs in the control group. There were no macroscopic small intestinal lesions observed in dogs receiving the 3X dose. Renal enlargement was reported during the necropsy of two dogs receiving the 3X and two receiving the 5X dose.

Microscopic examination of the kidneys revealed minimal degeneration or slight necrosis at the tip of the papilla in three dogs at the 5X dose. Microscopic examination of the stomach showed inflammatory mucosal lesions, epithelial regenerative hyperplasia or atrophy, and submucosal gland inflammation in two dogs at the recommended dose, three dogs at the 3X and four dogs at the 5X dose. Small intestinal microscopic changes included minimal focal mucosal erosion affecting the villi, and were sometimes associated with mucosal congestion. These lesions were observed in the ileum of one control dog and in the jejunum of one dog at the recommended dose and two dogs at the 5X dose.

Six Month Study

In a six month target animal safety study, meloxicam was administered orally at 1, 3, and 5X the recommended dose with no significant clinical adverse reactions. All animals in all dose groups (controls, 1, 3, and 5X the recommended dose) exhibited some gastrointestinal distress (diarrhea and vomiting). Treatment related changes seen in hematology and chemistry included decreased red blood cell counts in seven of 24 dogs (four 3X and three 5X dogs), decreased hematocrit in 18 of 24 dogs (including three control dogs), dose related neutrophilia in one 1X, two 3X and three 5X dogs, evidence of regenerative anemia in two 3X and one 5X dog. Also noted were increased BUN in two 5X dogs and decreased albumin in one 5X dog.

Endoscopic changes consisted of reddening of the gastric mucosal surface covering less than 25% of the surface area. This was seen in three dogs at the recommended dose, three dogs at the 3X dose and two dogs at the 5X dose. Two control dogs exhibited reddening in conjunction with ulceration of the mucosa covering less than 25% of the surface area.

Gross gastrointestinal necropsy results observed included mild discoloration of the stomach or duodenum in one dog at the 3X and in one dog at the 5X dose. Multifocal pinpoint red foci were observed in the gastric fundic mucosa in one dog at the recommended dose, and in one dog at the 5X dose.

No macroscopic or microscopic renal changes were observed in any dogs receiving meloxicam in this six month study. Microscopic gastrointestinal findings were limited to one dog at the recommended dose, and two dogs at the 3X dose. Mild inflammatory mucosal infiltrate was observed in the duodenum of one dog at the recommended dose. Mild congestion of the fundic mucosa and mild myositis of the outer mural musculature of the stomach were observed in two dogs receiving the 3X dose.

How Supplied:

METACAM Oral Suspension 0.5 mg/mL: 15 mL and 30 mL dropper bottles with measuring syringe.

NDC 0010-6014-01 – 0.5 mg/mL - 15 mL

NDC 0010-6014-02 – 0.5 mg/mL - 30 mL

Storage:

Store at controlled room temperature, 68 – 77°F (20 - 25°C). Excursions permitted between 59°F and 86°F (15°C and 30°C). Brief exposure to temperature up to 104°F (40°C) may be tolerated provided the mean kinetic temperature does not exceed 77°F (25°C); however such exposure should be minimized.

Approved by FDA under NADA # 141-213

Marketed by:
Boehringer Ingelheim Animal Health USA Inc.
Duluth, GA 30096

© 2022 Boehringer Ingelheim Animal Health USA Inc. All rights reserved.

METACAM is a registered trademark of Boehringer Ingelheim Vetmedica GmbH, used under license.

601413-06

1000001858

Revised 06/2022

Client Information Sheet for Metacam®

(meloxicam oral suspension) 0.5 mg/mL

Non-steroidal anti-inflammatory drug for oral use in dogs only

This summary contains important information about METACAM. You should read this information before you start giving your dog METACAM and review it each time the prescription is refilled. This sheet is provided only as a summary and does not take the place of instructions from your veterinarian. Talk to your veterinarian if you do not understand any of this information or if you want to know more about METACAM.

What Is METACAM?

METACAM is a prescription non-steroidal anti-inflammatory drug (NSAID) that is used to control pain and inflammation (soreness) due to osteoarthritis in dogs. Osteoarthritis (OA) is a painful condition caused by “wear and tear” of cartilage and other parts of the joints that may result in the following changes or signs in your dog: Limping or lameness, decreased activity or exercise (reluctance to stand, climb stairs, jump or run, or difficulty in performing these activities), stiffness or decreased movement of joints. METACAM is given to dogs by mouth. Do not use METACAM Oral Suspension in cats. Acute renal failure and death have been associated with the use of meloxicam in cats.

What Kind Of Results Can I Expect When My Dog Is On METACAM For OA?

While METACAM is not a cure for osteoarthritis, it can control the pain and inflammation of OA and improve your dog’s mobility.

• Response varies from dog to dog but can be quite dramatic.

• In most dogs, improvement can be seen in a matter of days.

• If METACAM is discontinued or not given as directed, your dog’s pain and inflammation may come back.

What Dogs Should Not Take METACAM?

Your dog should not be given METACAM if he/she:

• Has had an allergic reaction to meloxicam, the active ingredient of METACAM.

• Has had an allergic reaction (such as hives, facial swelling, or red or itchy skin) to aspirin or other NSAIDs.

• Is presently taking aspirin, other NSAIDs, or corticosteroids (unless directed by your veterinarian).

METACAM Should Only Be Given To Dogs

People should not take METACAM. Keep METACAM and all medication out of reach of children. Call your physician immediately if you accidentally take METACAM.

How To Give METACAM To Your Dog.

The actual dose to be given should be prescribed by the veterinarian.

Directions For Administration: Dogs under 10 pounds (4.5 kg)

Shake well before use, then remove cap. Particular care should be given with regard to the accuracy of dosing. To prevent accidental overdosing of small dogs, administer drops on food only, never directly into the mouth. Carefully measure suspension onto food to assure that the correct dose is given before presentation of the food to the dog. The syringe provided with the meloxicam concentration of

0.5 mg/mL cannot be used to measure doses for dogs weighing less than 2 lbs (0.90 kg).

For dogs less than 2 lbs (0.90 kg), METACAM Oral Suspension can be given using the dropper bottle: two drops for each pound of body weight for the 0.5 mg/mL concentration (five drops for each kilogram of body weight), dropped directly onto the food.

For dogs between 2 - 10 pounds, METACAM Oral Suspension can be given by drops or by using the measuring syringe provided in the package (see dosing procedure below). The syringe fits on to the bottle has a scale beginning at 2 lbs, designed to deliver the daily maintenance dose (0.05 mg/lb or 0.1 mg/kg). When using the syringe, the dog’s weight should be rounded down to the nearest 1 pound increment. Replace and tighten cap after use.

Dogs over 10 pounds (4.5 kg)

Shake well before use then remove cap. METACAM Oral Suspension may be either mixed with food or placed directly into the mouth. Particular care should be given with regard to the accuracy of dosing. METACAM Oral Suspension can be given using the measuring syringe provided in the package (see dosing procedure below). The syringe fits on to the bottle and has a scale in pounds designed to deliver the daily maintenance dose (0.05 mg/lb or 0.1 mg/kg). When using the syringe, the dog’s weight should be rounded down to the nearest 1 pound increment. Alternatively, METACAM Oral Suspension can be given using the dropper bottle: two drops for each pound of body weight for the 0.5 mg/mL concentration (five drops for each kilogram of body weight). Replace and tighten cap after use.

What To Tell/Ask Your Veterinarian Before Giving METACAM

Talk to your veterinarian about:

• The signs of OA you have observed (for example limping, stiffness).

• The importance of weight control and exercise in the management of OA.

• What tests might be done before METACAM is prescribed.

• How often your dog may need to be examined by your veterinarian.

• The risks and benefits of using METACAM.

Tell your veterinarian if your dog has ever had the following medical problems:

• Experienced side effects from METACAM or other NSAIDs, such as aspirin

• Digestive upset (vomiting and/or diarrhea)

• Liver disease

• Kidney disease

Tell your veterinarian about:

• Any other medical problems or allergies that your dog has now or has had.

• All medicines that you are giving your dog or plan to give your dog, including those you can get without a prescription.

Tell your veterinarian if your dog is:

• Pregnant, nursing or if you plan to breed your dog.

What Are The Possible Side Effects That May Occur In My Dog During METACAM Therapy?

METACAM, like other drugs, may cause some side effects. Serious but rare side effects have been reported in dogs taking NSAIDs. Serious side effects can occur with or without warning and in rare situations result in death.

The most common NSAID-related side effects generally involve the stomach and liver or kidney problems. Look for the following side effects that can indicate your dog may be having a problem with METACAM or may have another medical problem:

• Decrease or increase in appetite

• Vomiting

• Change in bowel movement (such as diarrhea, or black, tarry or bloody stools)

• Change in behavior (such as decreased or increased activity level, incoordination, seizure or aggression)

• Yellowing of gums, skin, or whites of the eyes (jaundice)

• Change in drinking habits (frequency, amount consumed)

• Change in urination habits (frequency, color, or smell)

• Change in skin (redness, scabs, or scratching)

It is important to stop therapy and contact your veterinarian immediately if you think your dog has a medical problem or side effect from METACAM therapy. If you have additional questions about possible side effects, talk to your veterinarian.

Can METACAM Be Given With Other Medicines?

METACAM should not be given with other NSAIDs (for example, aspirin, carprofen, etodolac, deracoxib) or steroids (for example, cortisone, prednisone, dexamethasone, triamcinolone).

Tell your veterinarian about all medicines you have given your dog in the past, and any medicines that you are planning to give with METACAM. This should include other medicines that you can get without a prescription.

Your veterinarian may want to check that all of your dog’s medicines can be given together.

What Can I Do In Case My Dog Eats More Than The Prescribed Amount?

Contact your veterinarian immediately if your dog eats more than the prescribed amount of METACAM.

What Else Should I Know About METACAM?

This sheet provides a summary of information about METACAM. If you have any questions or concerns about METACAM or osteoarthritis pain, talk to your veterinarian.

As with all prescribed medicines, METACAM should only be given to the dog for which it was prescribed. METACAM Oral Suspension is for use in dogs only. Do not give METACAM Oral Suspension to cats. It should be given to your dog only for the condition for which it was prescribed. It is important to periodically discuss your dog’s response to METACAM at regular check ups. Your veterinarian will best determine if your dog is responding as expected and if your dog should continue receiving METACAM.

For technical assistance or to report suspected adverse reactions, call 1-888-637-4251.

Marketed by:
Boehringer Ingelheim Animal Health USA Inc.
Duluth, GA 30096

METACAM is a registered trademark of Boehringer Ingelheim Vetmedica GmbH, used under license.

© 2022 Boehringer Ingelheim Animal Health USA Inc. All rights reserved.

601417-04

Revised 06/2022